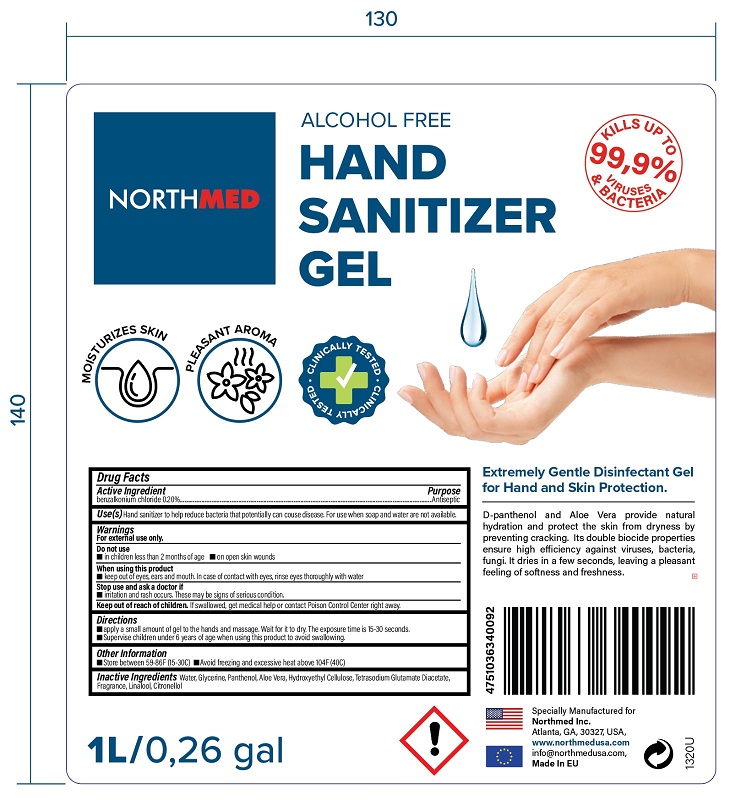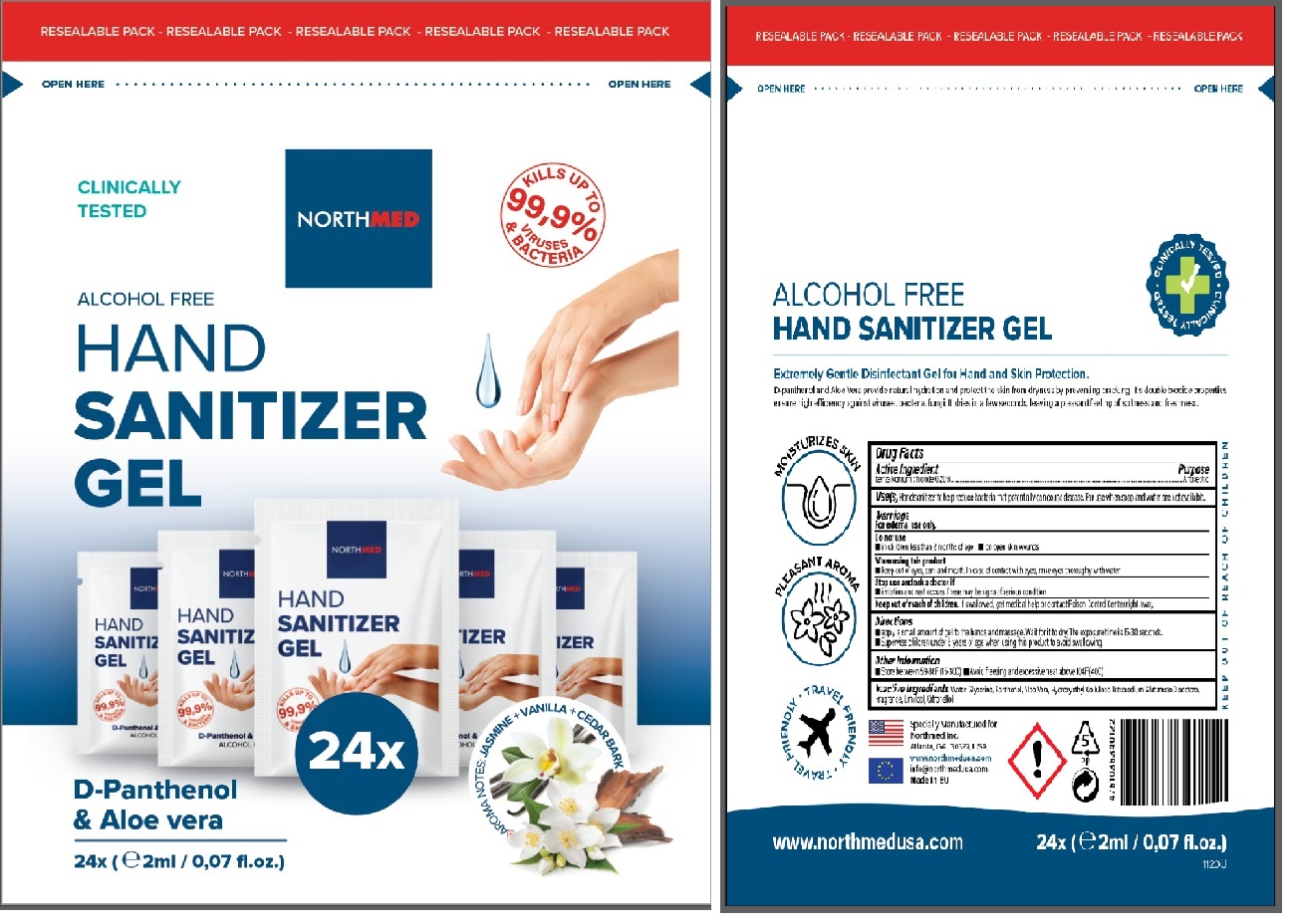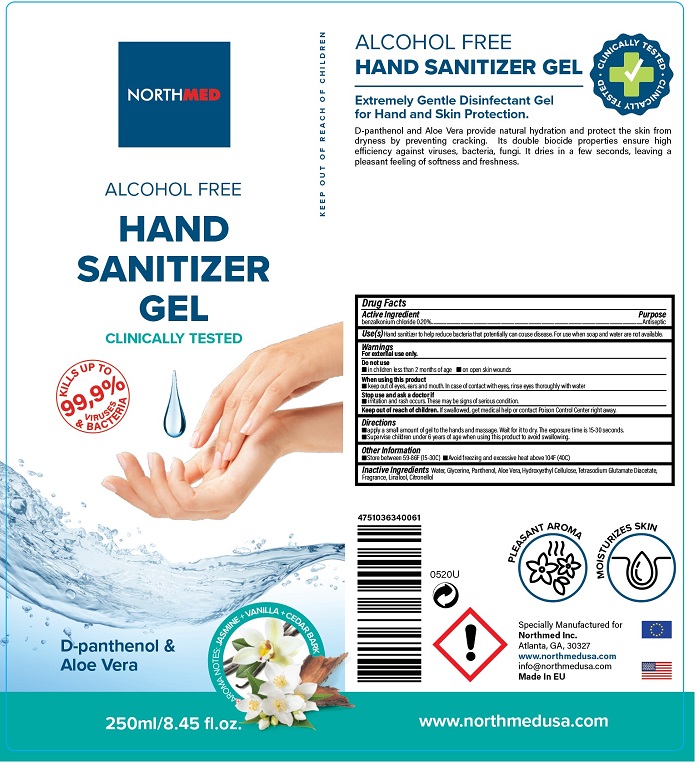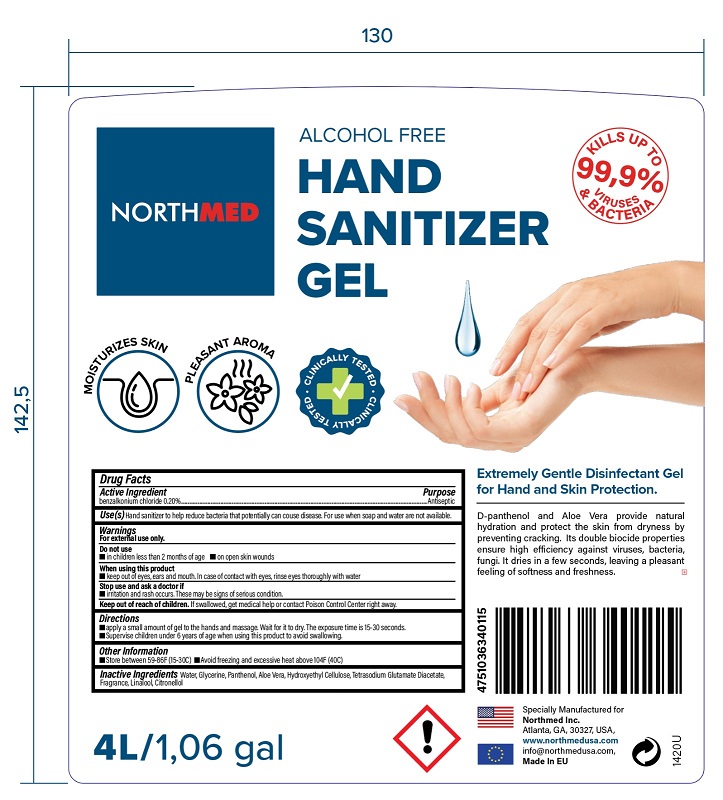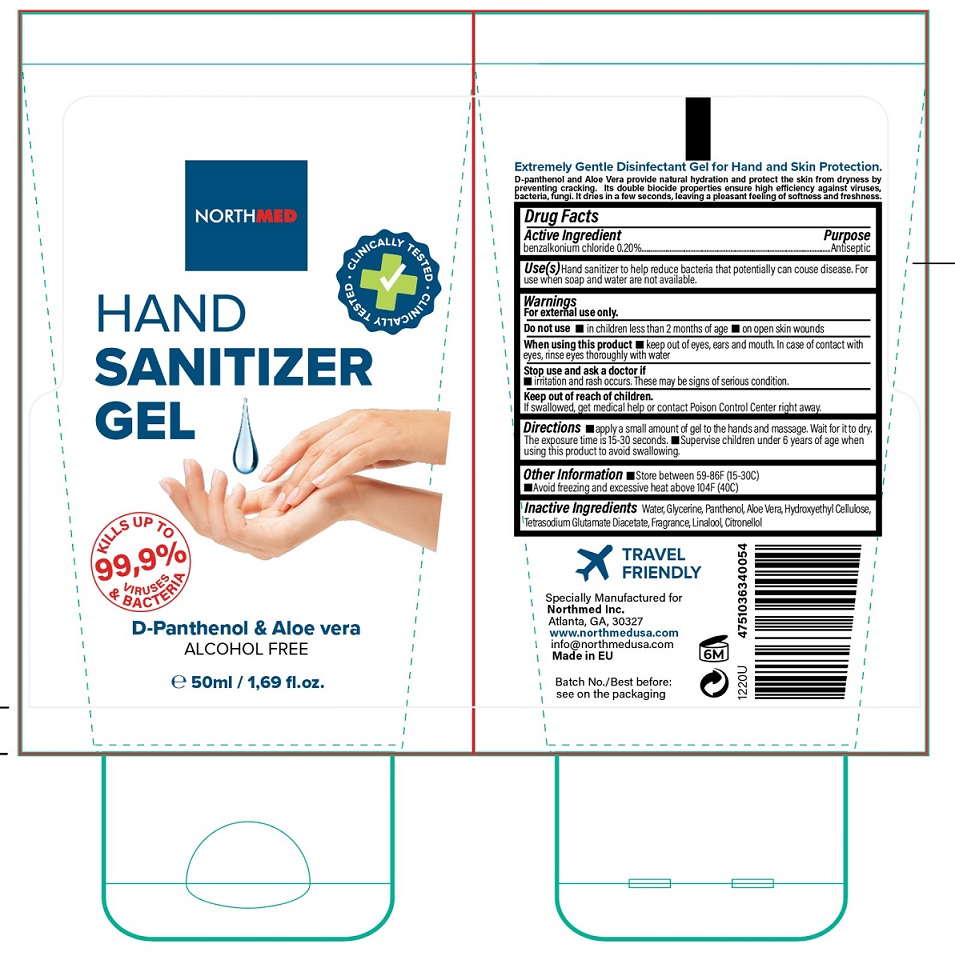 DRUG LABEL: Northmed Hand Sanitizer
NDC: 78522-010 | Form: GEL
Manufacturer: Northmed SIA
Category: otc | Type: HUMAN OTC DRUG LABEL
Date: 20200722

ACTIVE INGREDIENTS: BENZALKONIUM CHLORIDE 2 mg/1 mL
INACTIVE INGREDIENTS: WATER; GLYCERIN; PANTHENOL; HYDROXYETHYL CELLULOSE (140 MPA.S AT 5%); TETRASODIUM GLUTAMATE DIACETATE; LINALOOL, (+/-)-; .BETA.-CITRONELLOL, (+/-)-

Active Ingredient

Benzalkonium Chloride 0.2%

Purpose

Antiseptic

Use

Hand Sanitizer to help reduce bacteria that potentially can cause disease. For use when soap and water are not available.

Warnings

For external use only.

Do not use

- in children less than 2 months of age
- on open skin wounds

When using this product keep out of eyes, ears, and mouth. In case of contact with eyes, rinse eyes thoroughly with water.

Stop use and ask a doctor if irritation or rash occurs. These may be signs of a serious condition.

Keep out of reach of children. If swallowed, get medical help or contact a Poison Control Center right away.

Directions

- Apply a small amount of gel to hands and massage. Wait for it to dry. The exposure time is 15-0 seconds.
- Supervise children under 6 years of age when using this product to avoid swallowing.

Other information

- Store between 59-86F(15-30C)
- Avoid freezing and excessive heat above 104F (40C)

Inactive ingredients

Water, Glycerine, Panthenol, Aloe vera, Hydroxyethyl cellulose, Tetrasodium Glutamate Diacetate, Fragrance, Linalool, Citronellol

Package Label - Principal Display Panel

2 mL

50 mL

250 mL

1000 mL

4000 mL